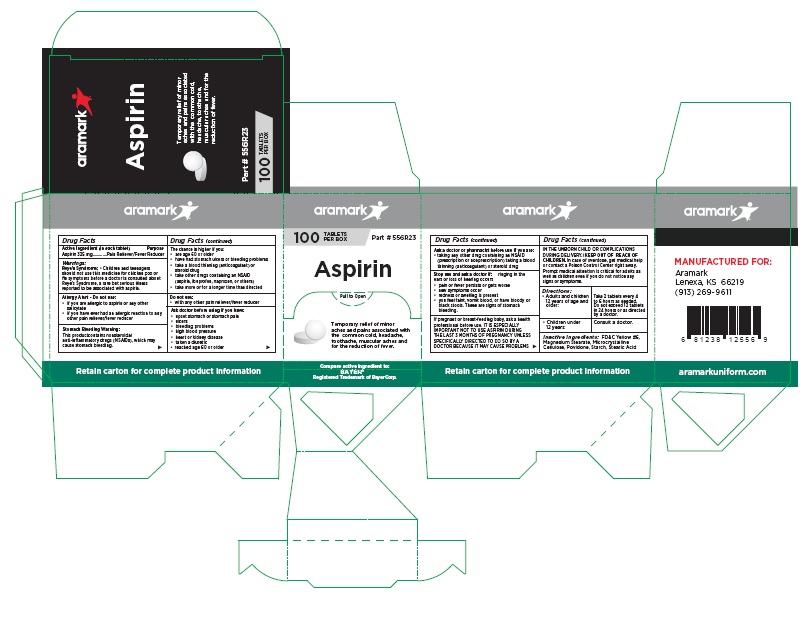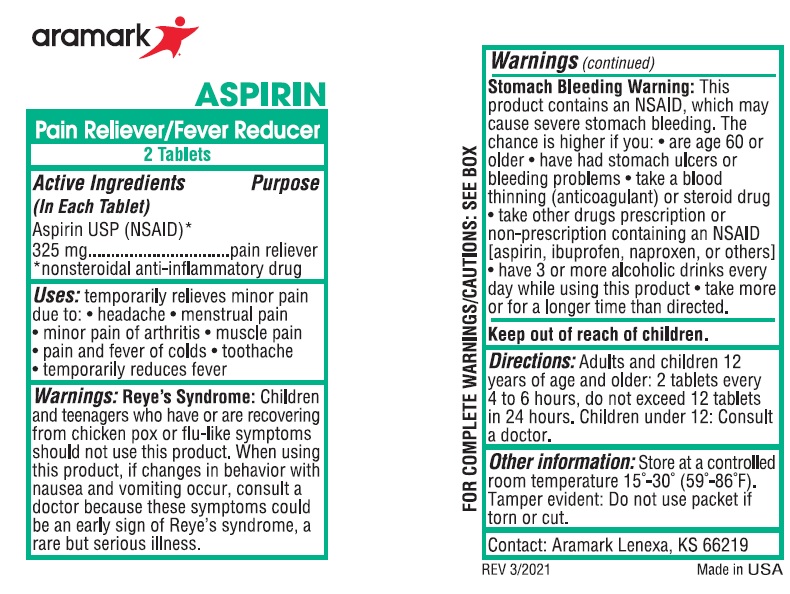 DRUG LABEL: Aramark Aspirin
NDC: 81238-0232 | Form: TABLET
Manufacturer: Western First Aid Safety DBA Aramark
Category: otc | Type: HUMAN OTC DRUG LABEL
Date: 20210519

ACTIVE INGREDIENTS: ASPIRIN 325 mg/1 1
INACTIVE INGREDIENTS: FD&C YELLOW NO. 6; MAGNESIUM STEARATE; MICROCRYSTALLINE CELLULOSE; POVIDONE; STARCH, CORN; STEARIC ACID

Aramark Aspirin

Drug Facts

Active Ingredients

(in Each Tablet)

Aspirin USP (NSAID)* 325 mg

*nonsteroidal anti-inflammatory drug

Purpose
Pain Reliever/Fever Reducer

INDICATIONS AND USAGE

Uses: temporarily relieves minor pain
due to: • headache • menstrual pain
• minor pain of arthritis • muscle pain
• pain and fever of colds • toothache
• temporarily reduces fever

Warnings:
Reye’s Syndrome: • Children and teenagers
should not use this medicine for chicken pox or
flu symptoms before a doctor is consulted about
Reye’s Syndrome, a rare but serious illness
reported to be associated with aspirin

Allergy Alert - Do not use:
• if you are allergic to aspirin or any other
salicylate
• if you have ever had an allergic reaction to any
other pain reliever/fever reducer

Stomach Bleeding Warning:
This product contains nonsteroidal
anti-inflammatory drugs (NSAIDs), which may
cause stomach bleeding.

The chance is higher if you:
• are age 60 or older
• have had stomach ulcers or bleeding problems
• take a blood thinning (anticoagulant) or
steroid drug
• take other drugs containing an NSAID
(aspirin, ibuprofen, naproxen, or others)
• take more or for a longer time than directed

Do not use:
• with any other pain reliever/fever reducer

Ask doctor before using if you have:
• upset stomach or stomach pain
• ulcers
• bleeding problems
• high blood pressure
• heart or kidney disease
• taken a diuretic
• reached age 60 or older

Ask a doctor or pharmacist before use if you are:
• taking any other drug containing an NSAID
(prescription or nonprescription) taking a blood
thinning (anticoagulant) or steroid drug

Stop use and ask a doctor if: ringing in the
ears or loss of hearing occurs
• pain or fever persists or gets worse
• new symptoms occur
• redness or swelling is present
• you feel faint, vomit blood, or have bloody or
black stools. These are signs of stomach
bleeding.

PREGNANCY OR BREAST FEEDING

If pregnant or breast-feeding baby, ask a health
professional before use. IT IS ESPECIALLY
IMPORTANT NOT TO USE ASPIRIN DURING
THE LAST 3 MONTHS OF PREGNANCY UNLESS
SPECIFICALLY DIRECTED TO DO SO BY A
DOCTOR BECAUSE IT MAY CAUSE PROBLEMS
IN THE UNBORN CHILD OR COMPLICATIONS
DURING DELIVERY.

KEEP OUT OF REACH OF CHILDREN.

In case of overdose, get medical help
or contact a Poison Control Center right away.
Prompt medical attention is critical for adults as
well as children even if you do not notice any
signs or symptoms.

DOSAGE AND ADMINISTRATION

Directions: • Adults and children 12 years of age and older: | Take 2 tablets every 4 to 6 hours as needed. Do not exceed 12 tablets in 24 hours or as directed by a doctor.
• Children under 12 years: | Consult a doctor.

Inactive Ingredients: FD&C Yellow #6,
Magnesium Stearate, Microcrystalline
Cellulose, Povidone, Starch, Stearic Acid

Product Package

aramark

Aspirin

Part # 556R23

100 TABLETS PER BOX

Compare active ingredient to:
BAYER®
Registered Trademark of Bayer Corp.

Retain carton for complete product information

MANUFACTURED FOR:
Aramark
Lenexa, KS 66219
(913) 269-9611

Box

Packet

res